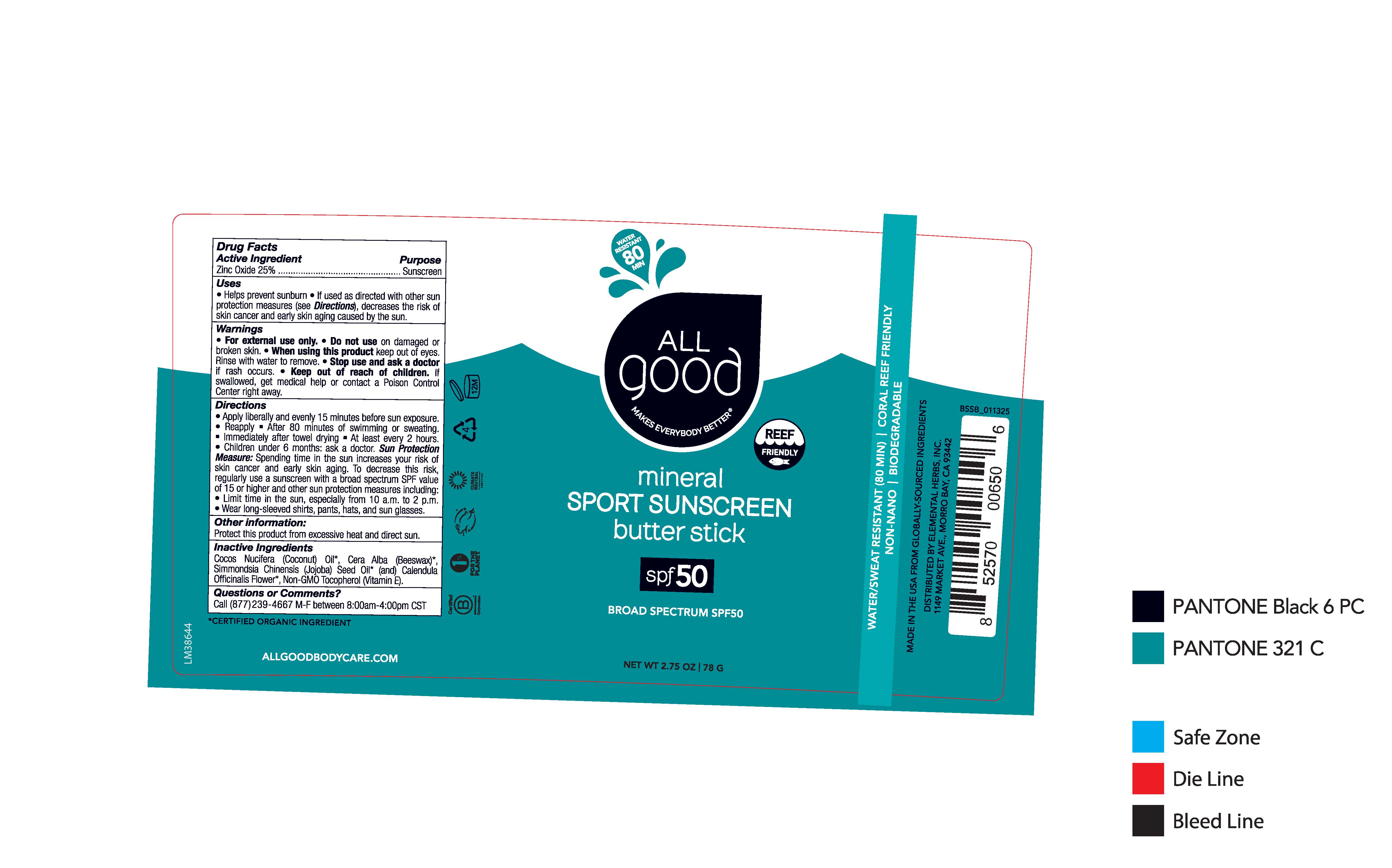 DRUG LABEL: All Good Mineral Sport Sunscreen Butter Stick SPF 50
NDC: 75786-229 | Form: OINTMENT
Manufacturer: Elemental Herbs, Inc.
Category: otc | Type: HUMAN OTC DRUG LABEL
Date: 20250505

ACTIVE INGREDIENTS: ZINC OXIDE 25 g/100 g
INACTIVE INGREDIENTS: COCONUT OIL; TOCOPHEROL; CALENDULA OFFICINALIS FLOWER; WHITE WAX; JOJOBA OIL

92204 All Good Mineral Sport Sunscreen Butter Stick SPF 50 (English-Only US Label)

Drug Facts

Active Ingredient

Zinc Oxide 25%

Uses

- Helps prevent sunburn
- if used as directed with other sun protection measures (see Directions), decreases the risk of skin cancer and early skin aging caused by the sun.

Warnings

- For external use only.

- Do not use on damaged or broken skin.

- When using this product keep out of eyes. Rinse with water to remove.

- Stop use and ask a doctor if rash occurs.

- Keep out of reach of children. If swallowed, get medical help or contact a Poison Control Center right away.

Directions

- Apply liberally/generously (and evenly) 15 minutes before sun exposure
- Reapply
- After 80 minutes of swimming or sweating
- Immediately after towel drying
- At least every 2 hours.
- Children under 6 months: ask a doctor

Sun Protection Measure: Spending time in the sun increases your risk of skin cancer and early skin aging. To decrease this risk, regularly use a sunscreen with a broad spectrum SPF value of 15 or higher and other un protection measures including:

- Limit time in the sun, especially from 10 a.m. to 2 p.m.
- Wear long-sleeved shirts, pants, hats, and sun glasses.

Other information:

Protect this product from excessive heat and direct sun.

Inactive Ingredients

Cocos Nucifera (Coconut) Oil*, Cera Alba (Beeswax)*, Simmondsia Chinensis (Jojoba) Seed Oil* 9and) Calendula Officinalis Flower*, Non-GMO Tocopherol (Vitamin E).

*CERTIFIED ORGANIC INGREDIENT

Questions or Commnets?

Call (877)239-4667 M-F between 8:00am-4:00pm CST

WATER RESISTANT 80 MIN

ALL GOOD

MAKES EVERYBODY BETTER

REEF FRIENDLY

mineral

SPORT SUNSCREEN

butter stick

spf 50

BROAD SPECTRUM SPF50

NET WT 2.75 OZ | 78 G

WATER /SWEAT RESISTANT (80 MIN) | CORAL REEF FRIENDLY

NON-NANO | BIODEGRADABLE

MADE IN THE USA FROM GLOBALLY -SOURCED INGREDIENTS

DISTRIBUTED BY ELEMENTAL HERBS, INC.

1149 MARKET AVE., MORRO BAY, CA 93442

ALLGOODBODYCARE.COM

RECENT MAJOR CHANGES

Artwork updated to remove bi-lingual text (for Canadian market). Label is now English-only for US market.

Purpose

Sunscreen